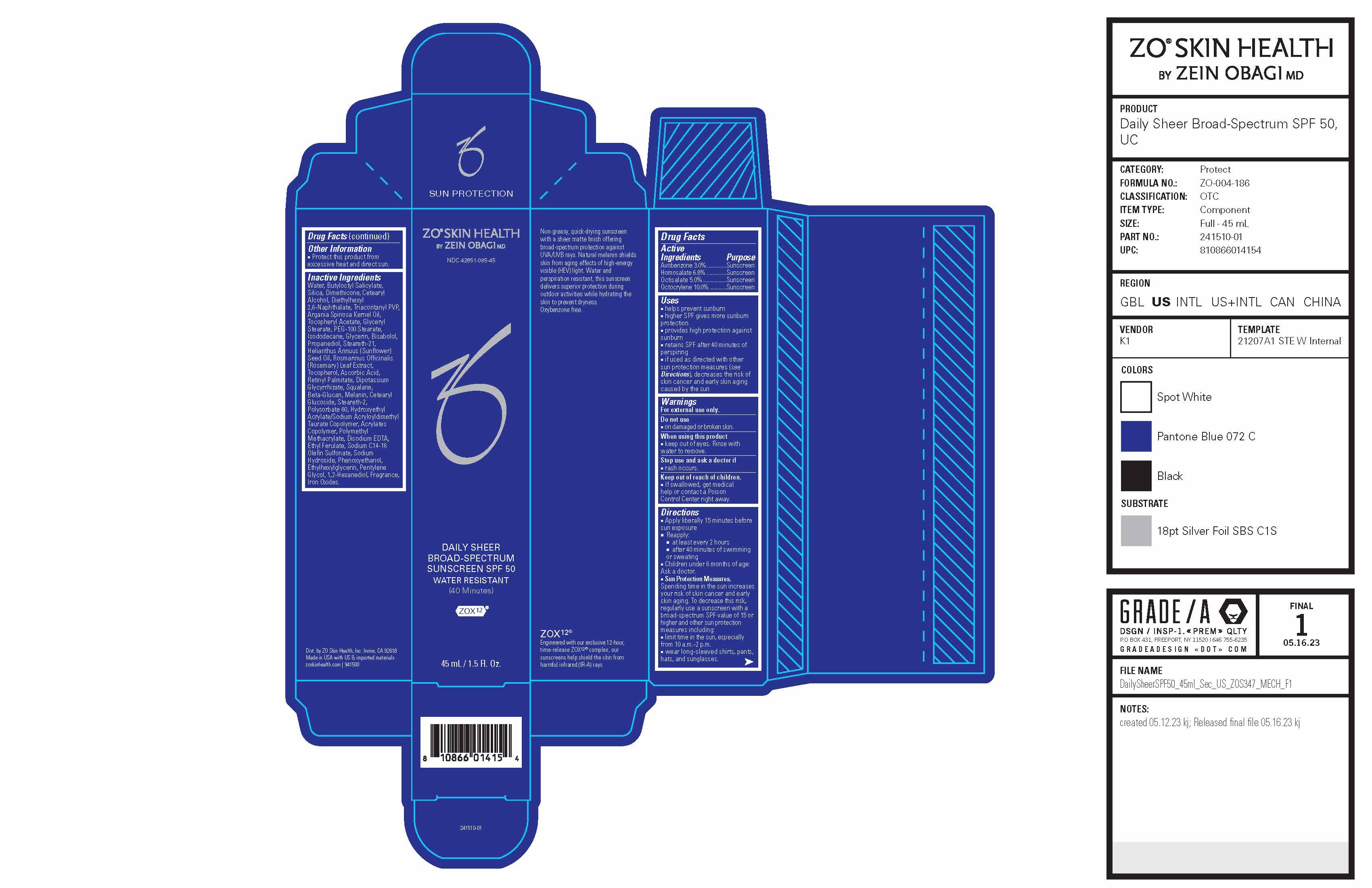 DRUG LABEL: ZO Skin Health Daily Sheer Broad-Spectrum Sunscreen SPF 50 Water Resistant (40 Minutes)
NDC: 42851-095 | Form: CREAM
Manufacturer: ZO Skin Health, Inc.
Category: otc | Type: HUMAN OTC DRUG LABEL
Date: 20241029

ACTIVE INGREDIENTS: HOMOSALATE 3060 mg/45 mL; OCTOCRYLENE 4500 mg/45 mL; OCTISALATE 2250 mg/45 mL; AVOBENZONE 1350 mg/45 mL
INACTIVE INGREDIENTS: PENTYLENE GLYCOL; 1,2-HEXANEDIOL; FERRIC OXIDE RED; WATER; SILICON DIOXIDE; TRIACONTANYL PVP (WP-660); ARGAN OIL; PEG-100 STEARATE; GLYCERIN; SUNFLOWER OIL; ASCORBIC ACID; SQUALANE; CETEARYL GLUCOSIDE; STEARETH-2; POLYSORBATE 60; HYDROXYETHYL ACRYLATE/SODIUM ACRYLOYLDIMETHYL TAURATE COPOLYMER (45000 MPA.S AT 1%); SODIUM HYDROXIDE; ETHYLHEXYLGLYCERIN; PHENOXYETHANOL; PROPANEDIOL; ROSEMARY; TOCOPHEROL; VITAMIN A PALMITATE; MELANIN SYNTHETIC (TYROSINE, PEROXIDE); POLY(METHYL METHACRYLATE; 450000 MW); EDETATE DISODIUM ANHYDROUS; SODIUM C14-16 OLEFIN SULFONATE; .ALPHA.-TOCOPHEROL ACETATE; GLYCERYL MONOSTEARATE; ISODODECANE; GLYCYRRHIZINATE DIPOTASSIUM; ETHYL FERULATE; LEVOMENOL; STEARETH-21; DIMETHICONE; CETOSTEARYL ALCOHOL; BUTYLOCTYL SALICYLATE; DIETHYLHEXYL 2,6-NAPHTHALATE

ZO® Skin Health Daily Sheer Broad-Spectrum Sunscreen SPF 50 Water Resistant (40 Minutes)
NDC 42851-095-45
Formula No. ZO-004-186

Drug Facts

Active Ingredients

Active Ingredients | Purpose
Avobenzone 3.0%............. | Sunscreen
Homosalate 6.8% ............. | Sunscreen
Octisalate 5.0%................ | Sunscreen
Octocrylene 10.0% ........... | Sunscreen

Uses

■ helps prevent sunburn
■ higher SPF gives more sunburn protection
■ provides high protection against sunburn
■ retains SPF after 40 minutes of perspiring
■ if used as directed with other sun protection measures (see Directions), decreases the risk of skin cancer and early skin aging caused by the sun

Warnings

For external use only.

Do not use

■ on damaged or broken skin.

When using this product

■ keep out of eyes. Rinse with water to remove.

Stop use and ask a doctor if

■ rash occurs.

Keep out of reach of children.

■ If swallowed, get medical help or contact a Poison Control Center right away.

Directions

■ Apply liberally 15 minutes before sun exposure
■ Reapply: ■ at least every 2 hours ■ after 40 minutes of swimming or sweating
■ Children under 6 months of age: Ask a doctor.
■ Sun Protection Measures. Spending time in the sun increases your risk of skin cancer and early skin aging. To decrease this risk, regularly use a sunscreen with a broad-spectrum SPF value of 15 or higher and other sun protection measures including:
■ limit time in the sun, especially from 10 a.m.-2 p.m.
■ wear long-sleeved shirts, pants, hats, and sunglasses.

Other Information

■ Protect this product from excessive heat and direct sun.

Inactive Ingredients

Water, Butyloctyl Salicylate, Silica, Dimethicone, Cetearyl Alcohol, Diethylhexyl 2,6-Naphthalate, Triacontanyl PVP, Argania Spinosa Kernel Oil, Tocopheryl Acetate, Glyceryl Stearate, PEG-100 Stearate, Isododecane, Glycerin, Bisabolol, Propanediol, Steareth-21, Helianthus Annuus (Sunflower) Seed Oil, Rosmarinus Officinalis (Rosemary) Leaf Extract, Tocopherol, Ascorbic Acid, Retinyl Palmitate, Dipotassium Glycyrrhizate, Squalane, Beta-Glucan, Melanin, Cetearyl Glucoside, Steareth-2, Polysorbate 60, Hydroxyethyl Acrylate/Sodium Acryloyldimethyl Taurate Copolymer, Acrylates Copolymer, Polymethyl Methacrylate, Disodium EDTA, Ethyl Ferulate, Sodium C14-16 Olefin Sulfonate, Sodium Hydroxide, Phenoxyethanol, Ethylhexylglycerin, Pentylene Glycol, 1,2-Hexanediol, Fragrance, Iron Oxides.

Principal Display Panel

ZO® Skin Health

by Zein Obagi MD

NDC 42851-095-45

Daily Sheer Broad-Spectrum Sunscreen SPF 50

Water Resistant

(40 Minutes)

ZOX12®

45 mL / 1.5 Fl. Oz.